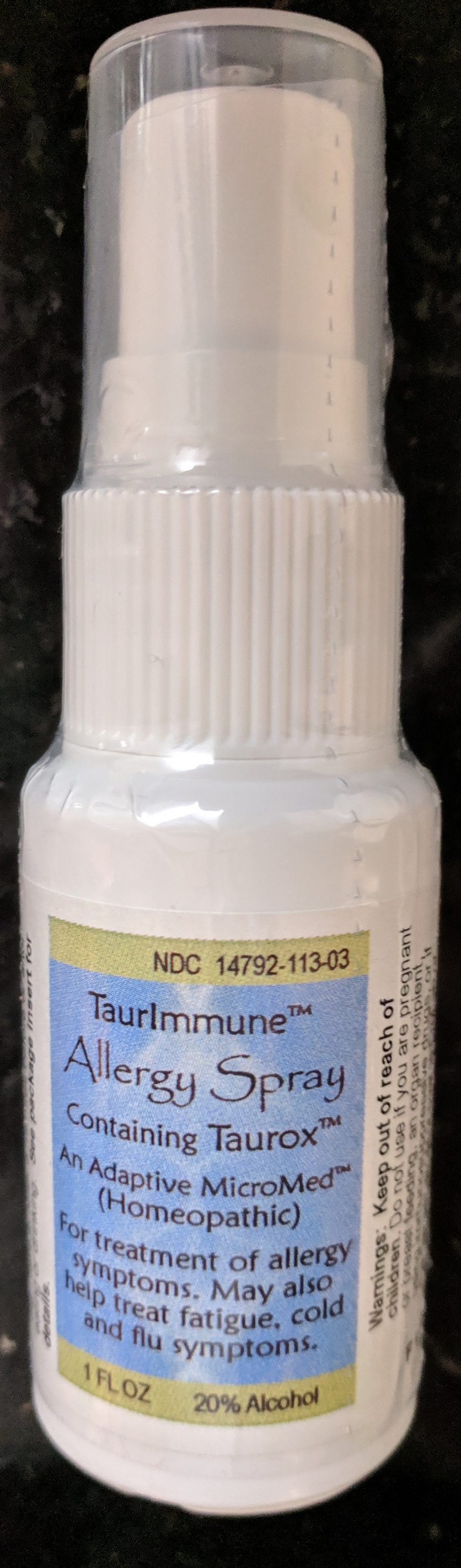 DRUG LABEL: TaurImmune Allergy
NDC: 73311-113 | Form: LIQUID
Manufacturer: CureImmune Corp.
Category: homeopathic | Type: HUMAN OTC DRUG LABEL
Date: 20190906

ACTIVE INGREDIENTS: ZINC 9 [hp_X]/1 1; ZINC CARBOBENZOXY-.BETA.-ALANYLTAURINATE 7 [hp_X]/1 1; PHOSPHORIC ACID 9 [hp_X]/1 1; SILICON DIOXIDE 9 [hp_X]/1 1; POTASSIUM CARBONATE 9 [hp_X]/1 1; SELENIUM 9 [hp_X]/1 1
INACTIVE INGREDIENTS: WATER; ALCOHOL

TaurImmune Allergy Spray

Active Ingredients

Tauroxicum 7X (26%), 12X (0.25%),30X (0.25%);

4.9% for each of the following:

Kali carb 9X, 12X, 30X,

Phosphoricum ac 9X, 12X, 30X,

Selenium 9X, 12X, 30X,

Silicea 9X, 12X, 30X,

Zinc met 9X, 12X, 30X.

Use

Immune support and treatment of allergy symptoms; fatigue, symptoms of colds, flu and other infections.

PURPOSE

Immune support and treatment of allergy symptoms; fatigue, symptoms of colds, flu and other infections.

Directions

Directions for adults and children 15 years of age and older: Take 4 sprays in mouth daily, or as directed by a health professional. Take at least 5 minutes before or after eating or drinking. See package insert for details.

Warnings

Keep out of reach of children. Do not use if you are pregnant or breast feeding, an organ recipient, using immunosuppressive drugs, or if the tamper-evident seal is broken or missing. See package insert for details.

Keep out of reach of children.

Inactive Ingredients

20% alcohol (ethanol), purified water

Disclaimer

Claims based on traditional
homeopathic practice, not accepted
medical evidence. Not FDA evaluated.

PACKAGE LABEL

TaurImmune

Allergy Spray

Containing Taurox

An Adaptive MicroMed

For treatment of allergy symptoms.

Also helps treat

cold & flu symptoms

and fatigue.

Homeopathic

1 FL OZ 20% alcohol